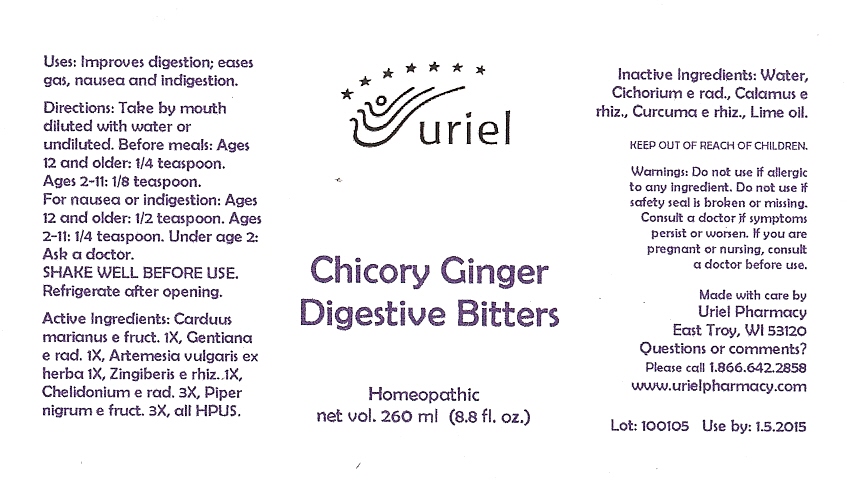 DRUG LABEL: Chicory Ginger Digestive Bitters
NDC: 48951-3083 | Form: LIQUID
Manufacturer: Uriel Pharmacy Inc
Category: homeopathic | Type: HUMAN OTC DRUG LABEL
Date: 20100224

ACTIVE INGREDIENTS: SILYBUM MARIANUM SEED 1 [hp_X]/1 1; GENTIANA LUTEA ROOT 1 [hp_X]/1 1; ARTEMISIA VULGARIS ROOT 1 [hp_X]/1 1; GINGER 1 [hp_X]/1 1; CHELIDONIUM MAJUS 3 [hp_X]/1 1; BLACK PEPPER 3 [hp_X]/1 1
INACTIVE INGREDIENTS: WATER; ACORUS CALAMUS; CURCUMA ZEDORIA ROOT; LIME OIL

Chicory Ginger Digestive Bitters - 8.8 oz.

Purpose

Uses: Improves digestion; eases gas, nausea and indigestion.

Dosage & Administration

Directions: Take by mouth diluted with water or undiluted. Before meals: Ages 12 and older: 1/4 teaspoon. Ages 2-11: 1/8 teaspoon. For nausea or indigestion: Ages 12 and older: 1/2 teaspoon. Ages 2-11: 1/4 teaspoon. Under age 2: Ask a doctor. SHAKE WELL BEFORE USE. Refrigerate after opening.

OTC-Active Ingredient

Active Ingredients: Carduus marianus e fruct. 1X, Gentiana e rad. 1X, Artemesia vulgaris ex herba 1X, Zingiberis e rhiz. 1X, Chelidonium e rad. 3X, Piper nigrum e fruct. 3X, all HPUS.

Inactive Ingredient

Inactive Ingredients: Water, Cichorium e rad., Calamus e rhiz., Curcuma e rhiz., Lime oil.

Keep out of reach of children

Do not use section

Warnings:Do not use if allergic to any ingredient. Do not use if safety seal is broken or missing.

Ask doctor section

Consult a doctor if symptoms persist or worsen.

Pregnancy or breast feeding section

If you are pregnant or nursing, consult a doctor before use.

Questions section

Made with care by
Uriel Pharmacy
East Troy, WI 53120
Questions or comments?
Please call 1.866.642.2858
www.urielpharmacy.com

Principal Display Panel

Chicory Ginger

Digestive Bitters

Homeopathic

net vol. 260 ml (8.8 fl. oz.)